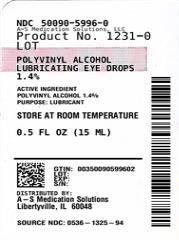 DRUG LABEL: Rugby Lubricating Drops
NDC: 50090-5996 | Form: SOLUTION/ DROPS
Manufacturer: A-S Medication Solutions
Category: otc | Type: HUMAN OTC DRUG LABEL
Date: 20231110

ACTIVE INGREDIENTS: POLYVINYL ALCOHOL 14 mg/1 mL
INACTIVE INGREDIENTS: SODIUM PHOSPHATE, DIBASIC, UNSPECIFIED FORM; EDETATE DISODIUM; SODIUM PHOSPHATE, MONOBASIC, UNSPECIFIED FORM; SODIUM CHLORIDE; WATER; BENZALKONIUM CHLORIDE

Rugby Lubricating Eye Drops

Active ingredient

Polyvinyl Alcohol 1.4%

Purpose

Lubricant

Uses

- for temporary relief of discomfort due to minor irritations of the eye or to exposure to wind or sun
- for use as a protectant against further irritation

Warnings

- Do not use if solution changes color or becomes cloudy

When using this product

- do not touch tip of container to any surface to avoid contamination
- remove contact lens before using.
- replace cap after using.
- keep container tightly closed

Stop use and ask a doctor if

- you experience eye pain, changes in vision, continued redness or irritation of the eye
- condition worsens or persists for more than 72 hours

Keep out of reach of children.

If swallowed, get medical help or contact a Poison Control Center right away

Directions

- instill 1 to 2 drops in the affected eye(s) as needed

Other information

- store at room temperature
- keep tightly closed
- replace cap after use
- retain carton for full drug facts

Inactive ingredients

dibasic sodium phosphate, edetate disodium, monobasic sodium phosphate,

purified water, sodium chloride. Phosphoric acid and/or sodium hydroxide may be added to adjust pH. PRESERVATIVE ADDED: benzalkonium chloride 0.01%

Questions ?

Call 1-800-645-2158

HOW SUPPLIED

Product: 50090-5996

NDC: 50090-5996-0 15 mL in a BOTTLE